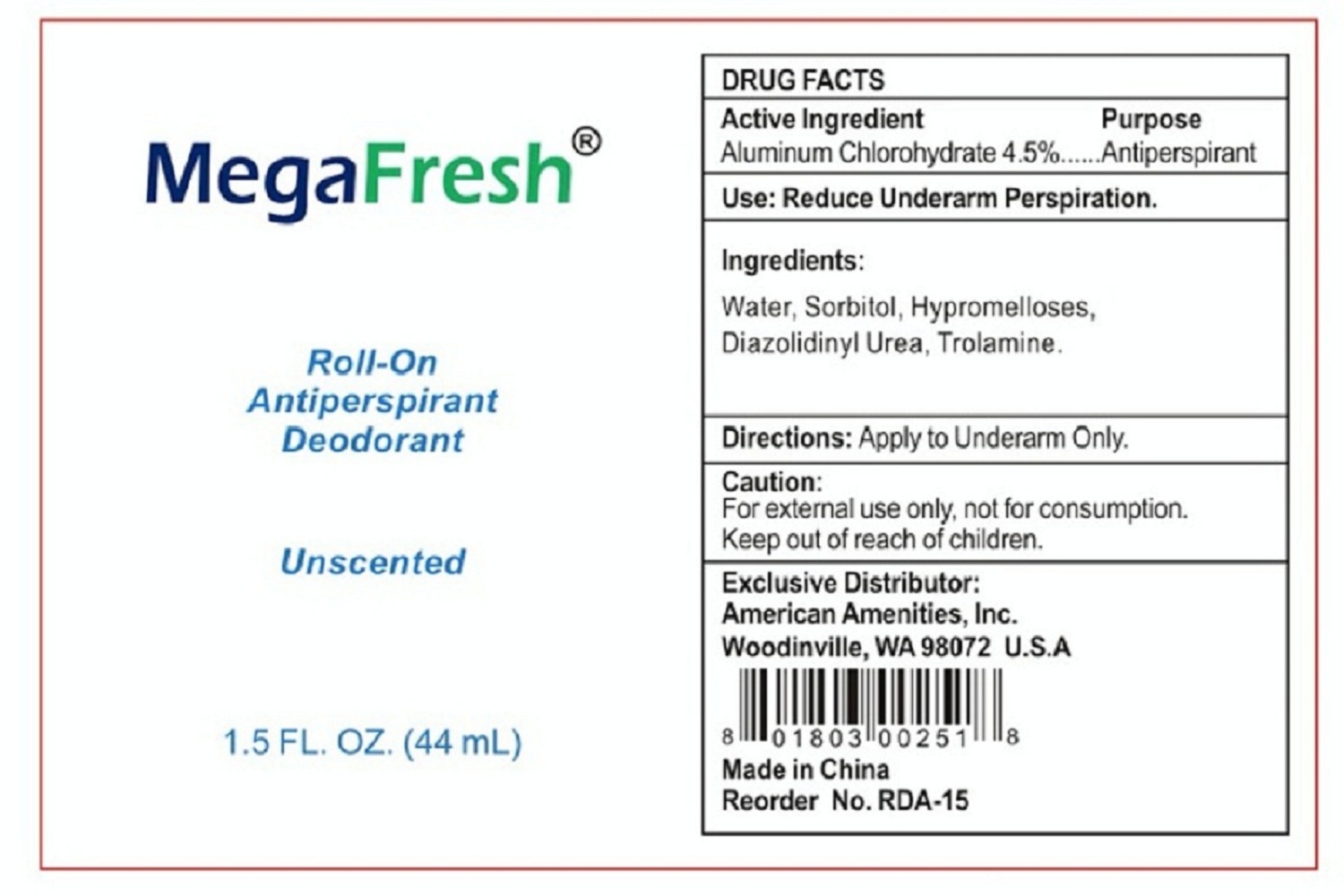 DRUG LABEL: MegaFresh Antiperspirant Roll-on Deodorant
NDC: 54157-107 | Form: LIQUID
Manufacturer: American Amenities, Inc.
Category: otc | Type: HUMAN OTC DRUG LABEL
Date: 20160112

ACTIVE INGREDIENTS: ALUMINUM CHLOROHYDRATE 4.5 g/100 mL
INACTIVE INGREDIENTS: WATER 4.5 g/100 mL; TROLAMINE; HYPROMELLOSES; SORBITOL; DIAZOLIDINYL UREA

Drug Fact

Active Ingredient

Aluminum Chlorohydrate 4.5%

Purpose

Antiperspirant

Uses

Reduce underarm perspiration

WARNINGS

Caution:

For external use only, not for consumption

Keep out of reach of children.

Directions

Apply to Underarm Only

Inactive Ingredient:

Water, Sorbitol, Hypromelloses, Diazolidinyl Urea, Trolamine